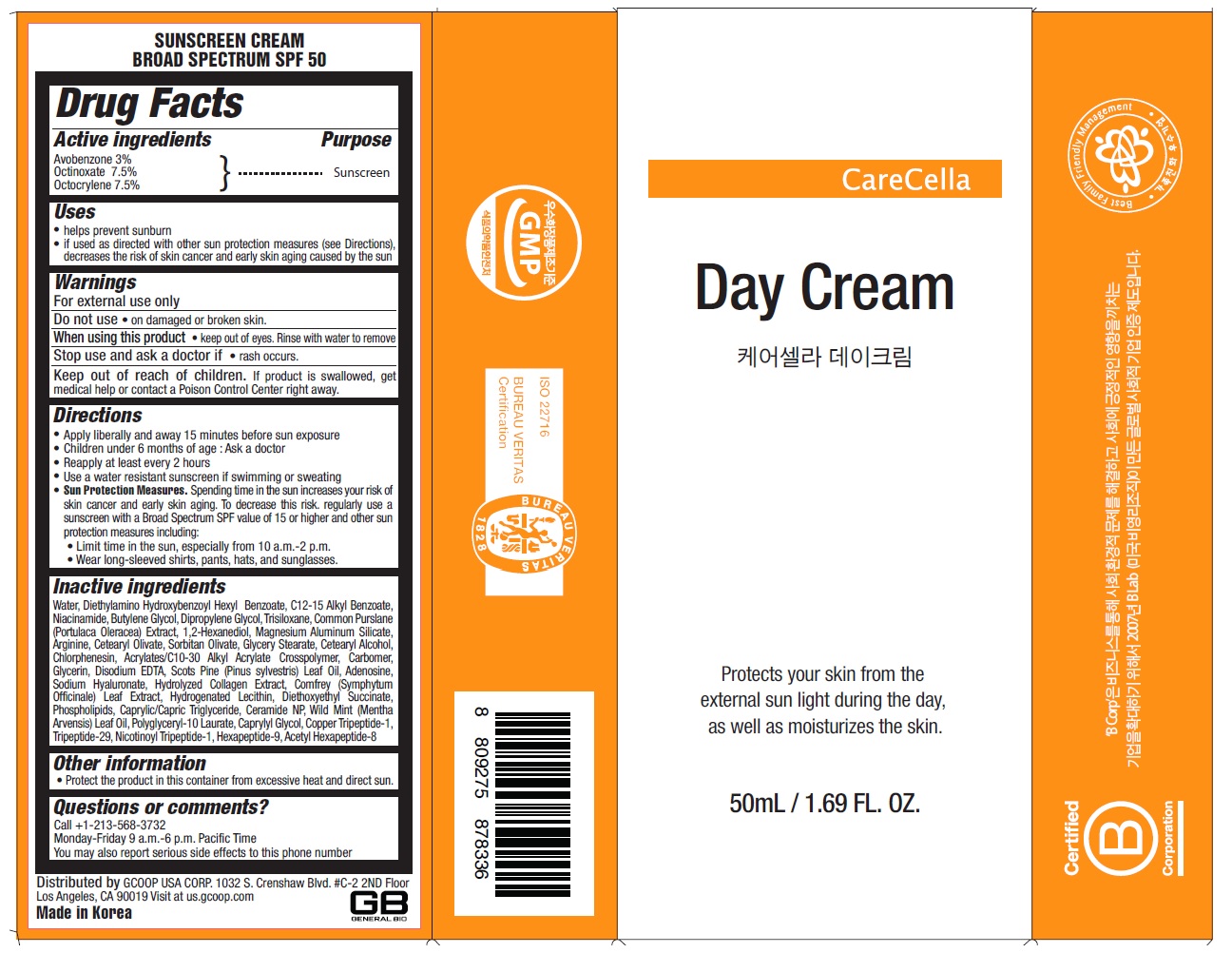 DRUG LABEL: CareCella
NDC: 69422-1302 | Form: CREAM
Manufacturer: General Bio Co., Ltd.
Category: otc | Type: HUMAN OTC DRUG LABEL
Date: 20171229

ACTIVE INGREDIENTS: AVOBENZONE 3 g/100 mL; OCTINOXATE 7.5 g/100 mL; OCTOCRYLENE 7.5 g/100 mL
INACTIVE INGREDIENTS: WATER; DIETHYLAMINO HYDROXYBENZOYL HEXYL BENZOATE; ALKYL (C12-15) BENZOATE; NIACINAMIDE; BUTYLENE GLYCOL; DIPROPYLENE GLYCOL; TRISILOXANE; PURSLANE; 1,2-HEXANEDIOL; MAGNESIUM ALUMINUM SILICATE; ARGININE; CETEARYL OLIVATE; SORBITAN OLIVATE; GLYCERYL MONOSTEARATE; CETOSTEARYL ALCOHOL; CHLORPHENESIN; CARBOMER INTERPOLYMER TYPE A (ALLYL SUCROSE CROSSLINKED); CARBOXYPOLYMETHYLENE; GLYCERIN; EDETATE DISODIUM ANHYDROUS; PINE NEEDLE OIL (PINUS SYLVESTRIS); ADENOSINE; HYALURONATE SODIUM; HYDROLYSED MARINE COLLAGEN (ENZYMATIC; 2000 MW); COMFREY LEAF; HYDROGENATED SOYBEAN LECITHIN; DIETHOXYETHYL SUCCINATE; LECITHIN, SOYBEAN; MEDIUM-CHAIN TRIGLYCERIDES; CERAMIDE NP; MENTHA ARVENSIS LEAF OIL; POLYGLYCERYL-10 LAURATE; CAPRYLYL GLYCOL; PREZATIDE COPPER; ACV TRIPEPTIDE; NICOTINURIC ACID; HEXAPEPTIDE-10; ACETYL HEXAPEPTIDE-8

CareCella Day Cream

Active ingredients

Avobenzone 3%

Octinoxate 7.5%

Octocrylene 7.5%

Purpose

Sunscreen

Uses

• helps prevent sunburn

• if used as directed with other sun protection measures (see Directions), decreases the risk of skin cancer and early skin aging caused by the sun

Warnings

For external use only

Do not use • on damaged or broken skin.

When using this product • keep out of eyes. Rinse with water to remove

Stop use and ask a doctor if • rash occurs.

Keep out of reach of children. If product is swallowed, get medical help or contact a Poison Control Center right away.

Directions

• Apply liberally and evenly 15 minutes before sun exposure

• Children under 6 months of age: Ask a doctor

• Reapply at least every 2 hours

• Use a water resistant sunscreen if swimming or sweating

• Sun Protection Measures. Spending time in the sun increases your risk of skin cancer and early skin aging. To decrease this risk, regularly use a sunscreen with a Broad Spectrum SPF value of 15 or higher and other sun protection measures including:

• Limit time in the sun, especially from 10 a.m.- 2 p.m.

• Wear long-sleeved shirts, pants, hats, and sunglasses.

Inactive ingredients

Water, Diethylamino Hydroxybenzoyl Hexyl Benzoate, C12-15 Alkyl Benzoate, Niacinamide, Butylene Glycol, Dipropylene Glycol, Trisiloxane, Common Purslane (Portulaca Oleracea) Extract, 1,2-Hexanediol, Magnesium Aluminum Silicate, Arginine, Cetearyl Olivate, Sorbitan Olivate, Glyceryl Stearate, Cetearyl Alcohol, Chlorphenesin, Acrylates/C10-30 Alkyl Acrylate Crosspolymer, Carbomer, Glycerin, Disodium EDTA, Scots Pine (Pinus sylvestris) Leaf Oil, Adenosine, Sodium Hyaluronate, Hydrolyzed Collagen Extract, Comfrey (Symphytum Officinale) Leaf Extract, Hydrogenated Lecithin, Diethoxyethyl Succinate, Phospholipids, Caprylic/Capric Triglyceride, Ceramide NP, Wild Mint (Mentha Arvensis) Leaf Oil, Polyglyceryl-10 Laurate, Caprylyl Glycol, Copper Tripeptide-1, Tripeptide-29, Nicotinoyl Tripeptide-1, Hexapeptide-9, Acetyl Hexapeptide-8

Other information

• Protect the product in this container from excessive heat and direct sun.

Questions or comments?

Call +1-213-568-3732

Monday-Friday 9 a.m.-6 p.m. Pacific Time

You may also report serious side effects to this phone number

Protects your skin from the external sun light during the day, as well as moisturizes the skin.

SUNSCREEN CREAM
BROAD SPECTRUM SPF 50

Distributed by GCOOP USA CORP. 1032 S. Crenshaw Blvd. #C-2 2ND Floor Los Angeles, CA 90019 Visit at us.gcoop.com

GB GENERAL BIO

Made in Korea